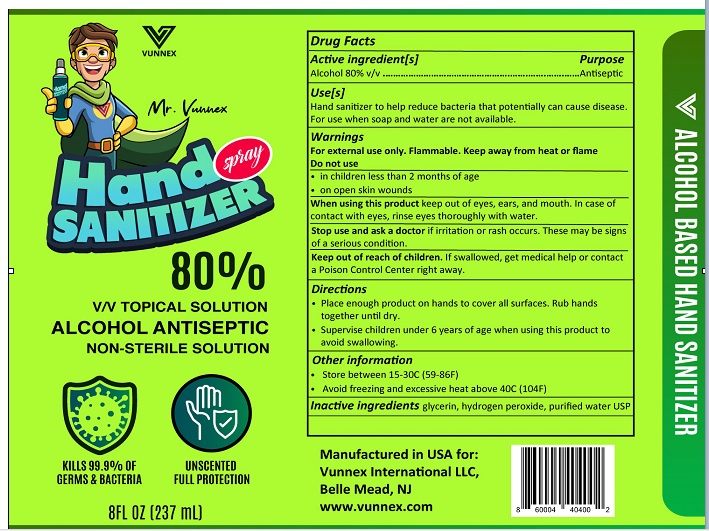 DRUG LABEL: VUNNEX Hand Sanitizer
NDC: 79450-001 | Form: LIQUID
Manufacturer: VUNNEX INTERNATIONAL LLC
Category: otc | Type: HUMAN OTC DRUG LABEL
Date: 20200630

ACTIVE INGREDIENTS: ALCOHOL 80 1/100 mL
INACTIVE INGREDIENTS: GLYCERIN; HYDROGEN PEROXIDE; WATER

Active Ingredient

Alcohol 80% v/v

Purpose

Antiseptic.

Warnings

For external use only. Flammable. Keep away from heat or flame.

Do not use• In children less than 2 months of age
• On open skin wounds

When using this product keep out of eyes, ears, and mouth. In case of contact rinse eyes thoroughly with water.

Stop use and ask a doctor

- if irritation or rash occurs.
- These may be signs of a serious condition.

Keep out of reach of children.

If swallowed, get medical help or contact a Poison Control Center right away.

Uses

Hand Sanitizer to help reduce bacteria that potentially can cause disease. For use when soap and water are not available.

Directions

- Place enough product on hands to cover all surfaces. Rub hands together until dry.
- Supervise children under 6 years of age when using this product to avoid swallowing.

Other Information

- Store between 15-30C (59-86F)
- Avoid freezing and excessive heat above 40C (104F)

Inactive ingredients

GLYCERIN,HYDROGEN PEROXIDE,WATER